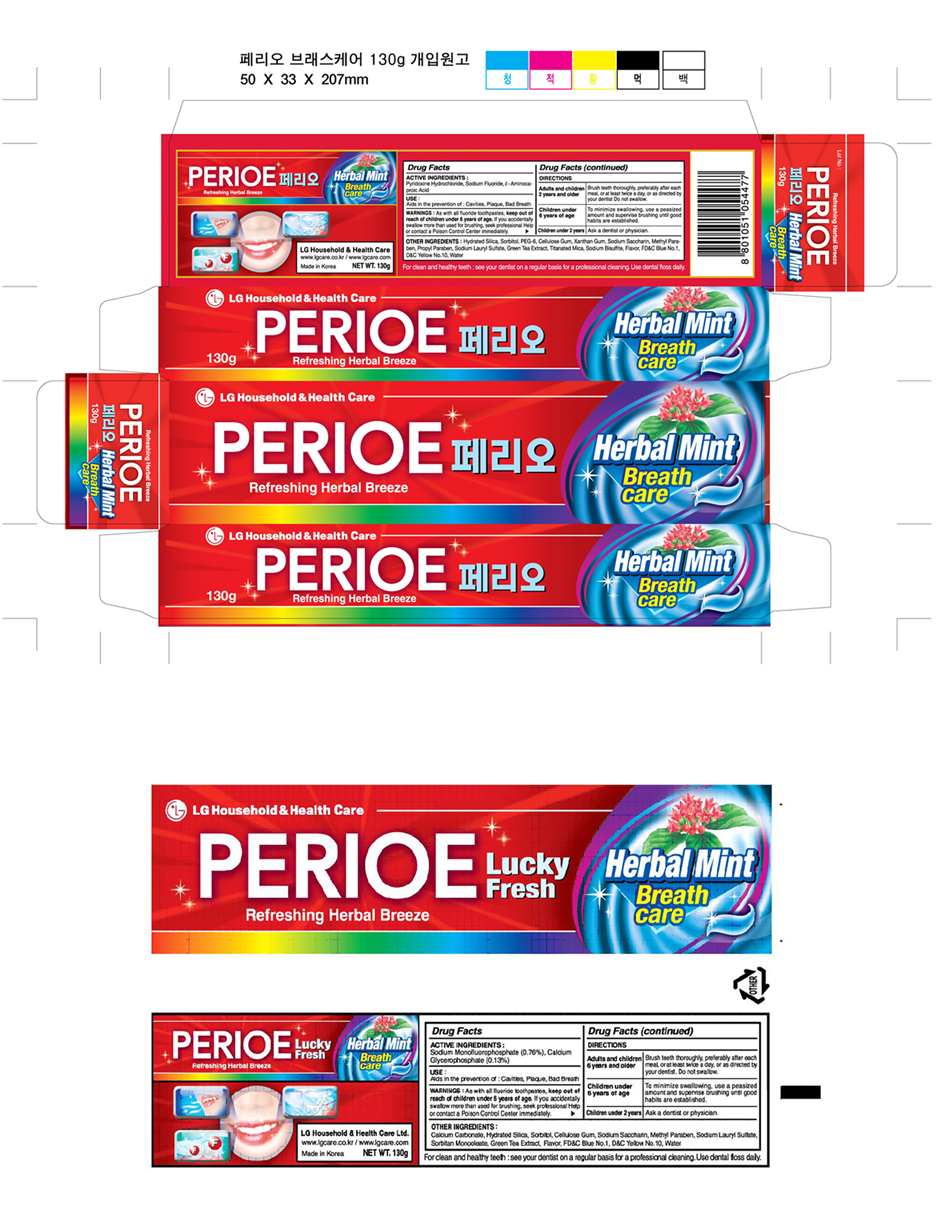 DRUG LABEL: Perioe lucky fresh - breath care
NDC: 53208-449 | Form: PASTE
Manufacturer: LG Household and Healthcare, Inc.
Category: otc | Type: HUMAN OTC DRUG LABEL
Date: 20100428

ACTIVE INGREDIENTS: Calcium Glycerophosphate .13 g/100 g; Sodium Monofluorophosphate .76 g/100 g
INACTIVE INGREDIENTS: Calcium Carbonate; SILICON DIOXIDE; Sorbitol; CARBOXYMETHYLCELLULOSE SODIUM; SACCHARIN SODIUM; Methylparaben; Sodium Lauryl Sulfate; Sorbitan Monooleate; GREEN TEA LEAF; FD&C BLUE NO. 1; D&C YELLOW NO. 10; Water

Drug Facts

ACTIVE INGREDIENT

Sodium Monofluorophosphate 0.76%
Calcium Glycerophosphate 0.13%

PURPOSE

Aids in the prevention of : Cavity, Plaque, Bad Breath

WARNINGS AND PRECAUTIONS

As with all fluoride toothpastes, keep out of reach of children under 6 years of age. If you accidentally swallow more than used for brushing, seek professional help or contact a Poison Control Center immediately.

DOSAGE AND ADMINISTRATION

Adults and children 6 years of age and older: brush teeth thoroughly, preferably after each meal or at least twice a day, or
as directed by a dentist. Do not swallow.
Children under 6 years of age: To minimize swallowing, use a peasized amount and supervise brushing until good habits are established.
Children under 2 years: Ask a dentist or physician.

PACKAGE LABEL

PERIO Lucky Fresh

Herbal Mint Breath Care

Refreshing Herbal Breeze